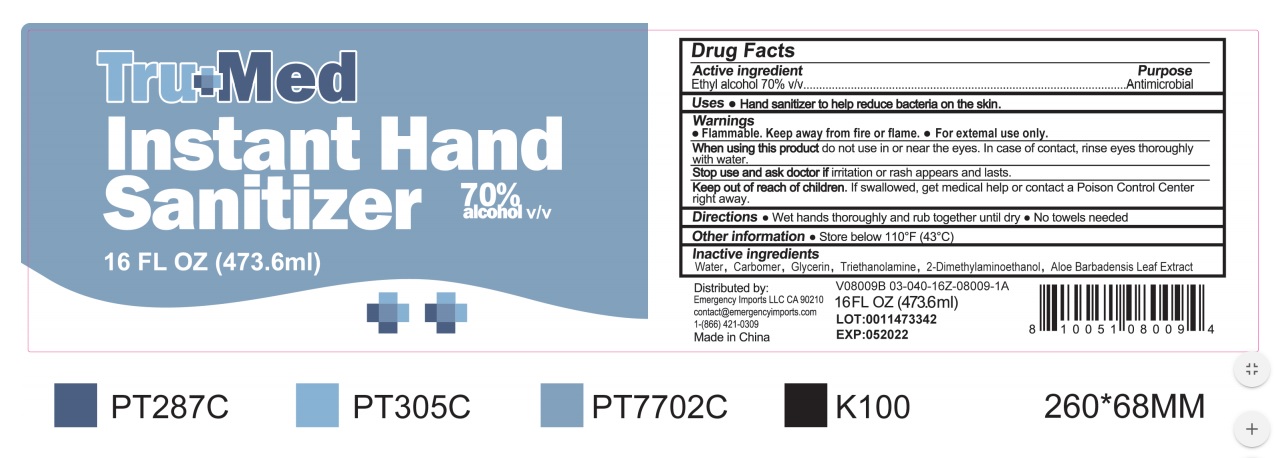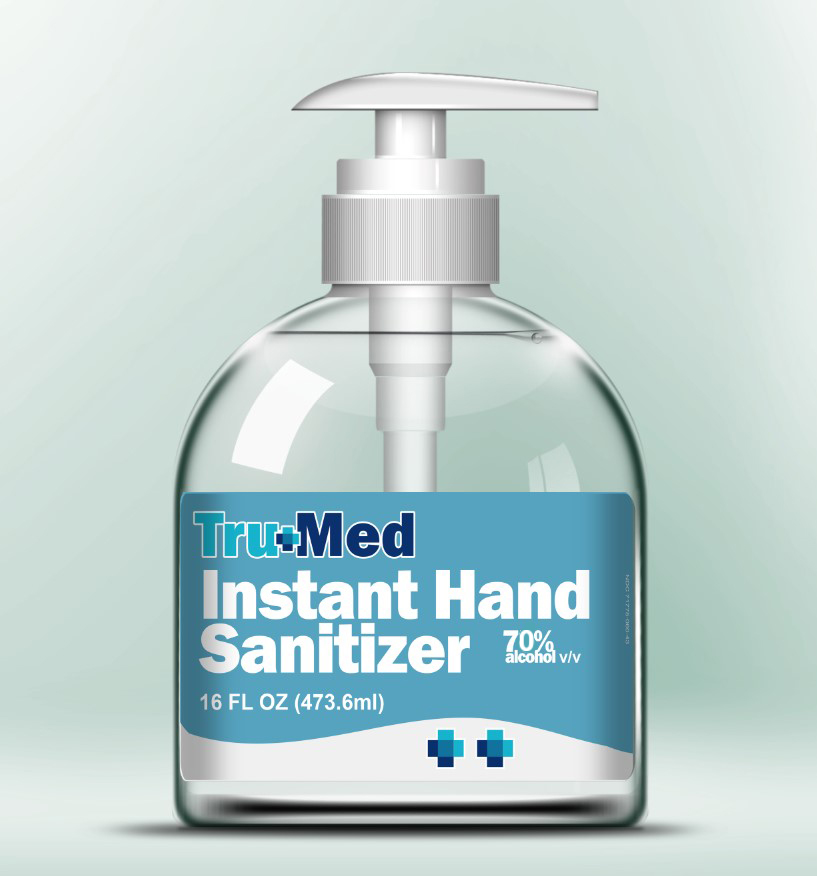 DRUG LABEL: TRUMED Hand Sanitizer
NDC: 70708-009 | Form: GEL
Manufacturer: GURUNANDA, LLC
Category: otc | Type: HUMAN OTC DRUG LABEL
Date: 20210611

ACTIVE INGREDIENTS: ALCOHOL 70 mL/100 mL
INACTIVE INGREDIENTS: TROLAMINE 0.1 mL/100 mL; WATER 27.585 mL/100 mL; GLYCERIN 0.01 mL/100 mL; CARBOMER 940 0.3 mg/100 mL; ALOE 0.0025 mL/100 mL; DEANOL 0.002 mL/100 mL

HAND SANITIZER

Active Ingredient

Ethyl Alcohol 70% v/v

PURPOSE

Antiseptic

WARNINGS

Flamable. Keep away from fire or flame.

For external use only.

When using this product do not use in or near the eyes. In case of contact , rinse eyes thoroughly with water.

Stop use and ask doctor if irritation or rash appears.

Keep out of reach of children. If swallowed, get medical help or contact a Poison Control Center rright away.

DOSAGE AND ADMINISTRATION

Wet hands thoroughly and rub together until dry. No towels needed.

OTHER SAFETY INFORMATION

Store below 110 F (43 C)

INACTIVE INGREDIENT

Water, Carbomer, Glycerin, Triethanolamine, 2-Dimethylaminoethanol, Aloe Barbadensis leaf Extract.

INDICATIONS AND USAGE

Hand sanitizer to help reduce bacteria on the skin.